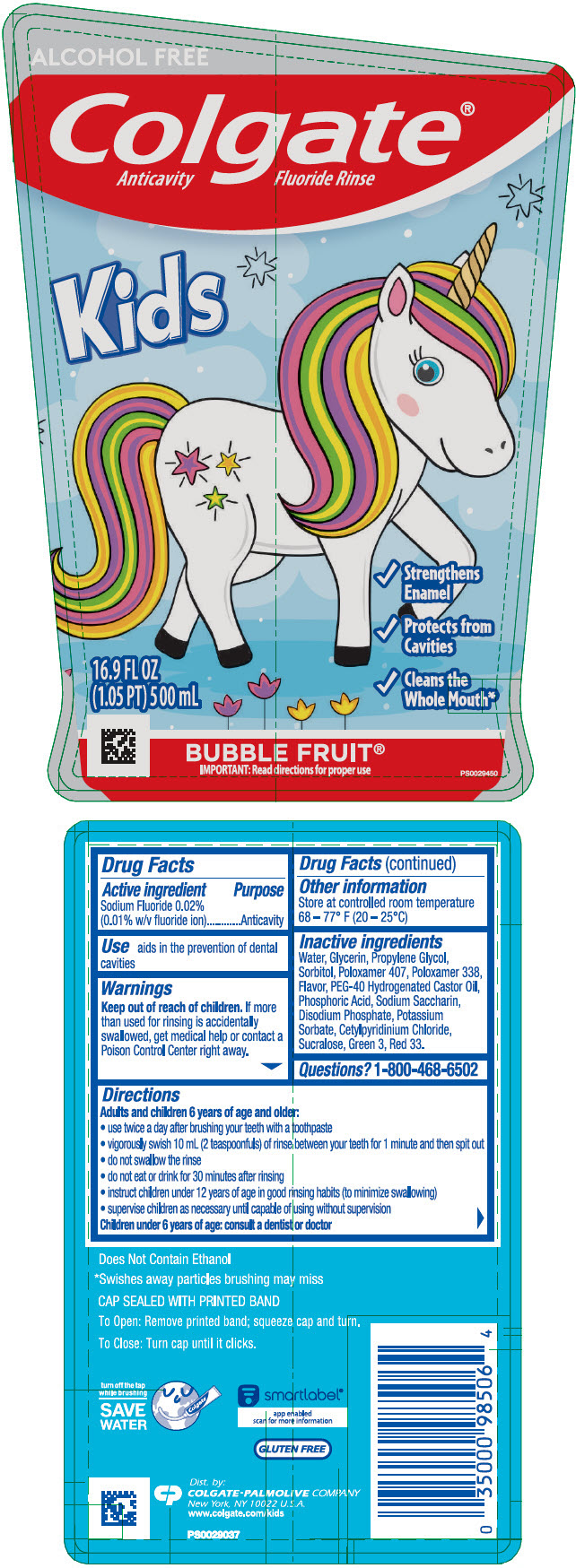 DRUG LABEL: Colgate Kids Unicorn Alcohol Free
NDC: 35000-334 | Form: RINSE
Manufacturer: Colgate-Palmolive Company
Category: otc | Type: HUMAN OTC DRUG LABEL
Date: 20240109

ACTIVE INGREDIENTS: SODIUM FLUORIDE 0.1 mg/1 mL
INACTIVE INGREDIENTS: WATER; GLYCERIN; PROPYLENE GLYCOL; SORBITOL; POLOXAMER 407; POLOXAMER 338; PEG-40 CASTOR OIL; PHOSPHORIC ACID; SACCHARIN SODIUM; SODIUM PHOSPHATE, DIBASIC, UNSPECIFIED FORM; POTASSIUM SORBATE; CETYLPYRIDINIUM CHLORIDE; SUCRALOSE; FD&C GREEN NO. 3; D&C RED NO. 33

Colgate® Kids Unicorn Alcohol Free

Drug Facts

Active ingredient

Sodium Fluoride 0.02% (0.01% w/v fluoride ion)

Purpose

Anticavity

Use

aids in the prevention of dental cavities

Warnings

Keep out of reach of children. If more than used for rinsing is accidentally swallowed, get medical help or contact a Poison Control Center right away.

Directions

Adults and children 6 years of age and older:

- use twice a day after brushing your teeth with a toothpaste
- vigorously swish 10 mL (2 teaspoonfuls) of rinse between your teeth for 1 minute and then spit out
- do not swallow the rinse
- do not eat or drink for 30 minutes after rinsing
- instruct children under 12 years of age in good rinsing habits (to minimize swallowing)
- supervise children as necessary until capable of using without supervison

Children under 6 years of age: consult a dentist or doctor

Other information

Store at controlled room temperature 68 – 77° F (20 – 25°C)

Inactive ingredients

Water, Glycerin, Propylene Glycol, Sorbitol, Poloxamer 407, Poloxamer 338, Flavor, PEG-40 Hydrogenated Castor Oil, Phosphoric Acid, Sodium Saccharin, Disodium Phosphate, Potassium Sorbate, Cetylpyridinium Chloride, Sucralose, Green 3, Red 33.

Questions?

1-800-468-6502

Dist. by:
COLGATE-PALMOLIVE COMPANY
New York, NY 10022 U.S.A.

PRINCIPAL DISPLAY PANEL - 500 mL Bottle Label

ALCOHOL FREE

Colgate®
Anticavity Fluoride Rinse

Kids

✓ Strengthens
  Enamel
✓ Protects from
  Cavities
✓ Cleans the
  Whole Mouth*

16.9 FL OZ
(1.05 PT) 500 mL

BUBBLE FRUIT®

IMPORTANT: Read directions for proper use

PS0029450